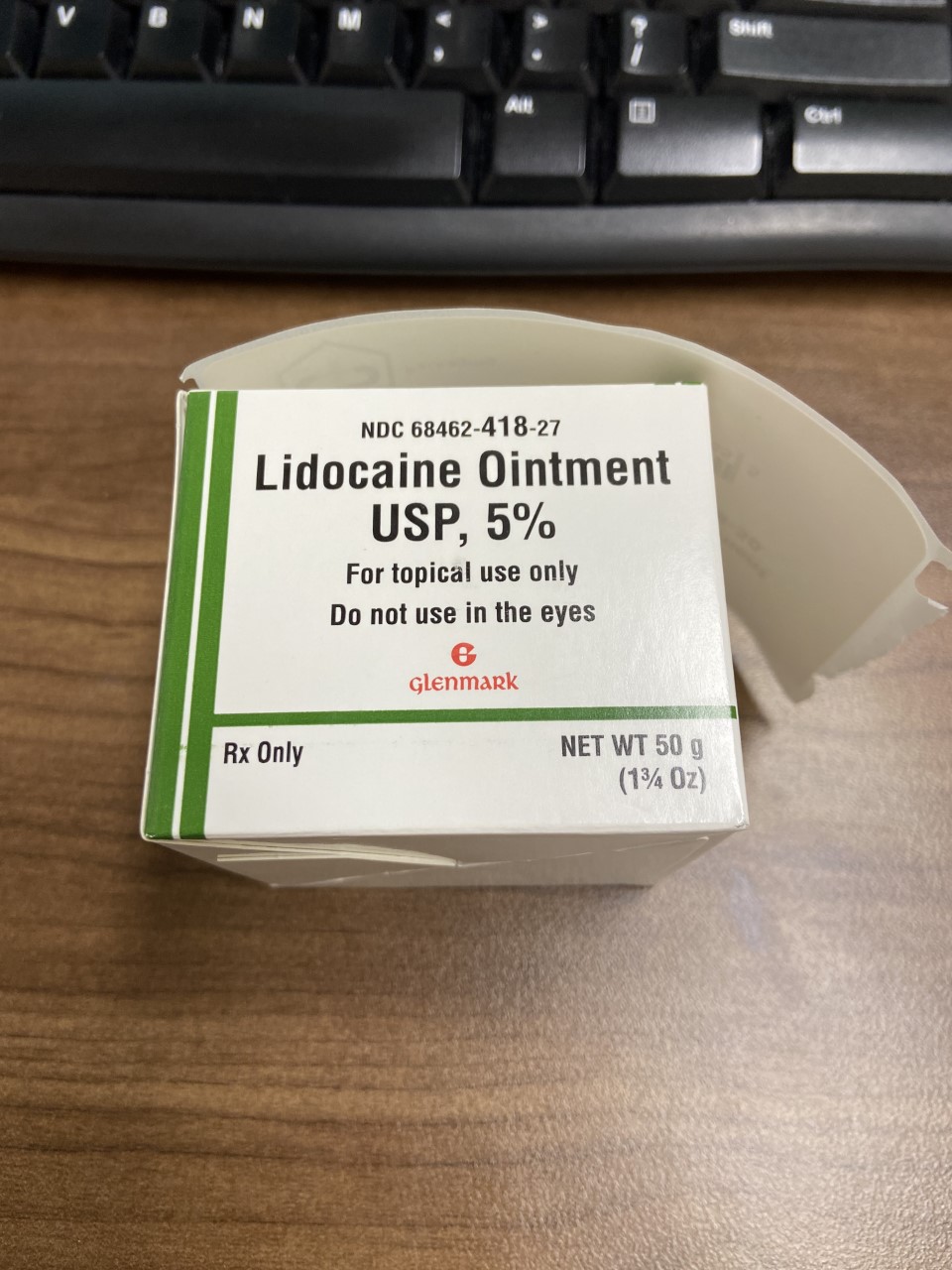 DRUG LABEL: LIDOCAINE
NDC: 80175-0418 | Form: OINTMENT
Manufacturer: Central Packaging
Category: prescription | Type: HUMAN PRESCRIPTION DRUG LABEL
Date: 20210302

ACTIVE INGREDIENTS: LIDOCAINE 50 mg/1 g

INDICATIONS AND USAGE

Lidocaine ointment, 5% is indicated for production of anesthesia of accessible mucous membranes of the oropharynx.

It is also useful as an anesthetic lubricant for intubation and for the temporary relief of pain associated with minor burns, including sunburn, abrasions of the skin, and insect bites